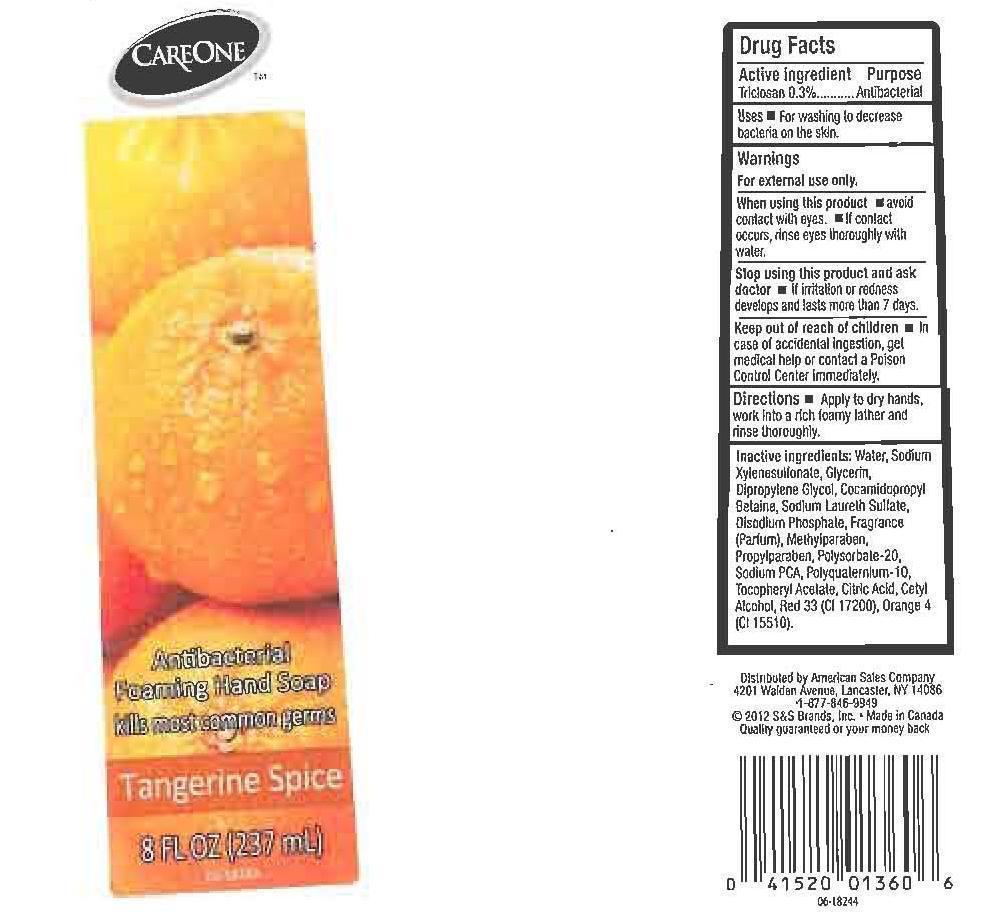 DRUG LABEL: CARE ONE
NDC: 41520-191 | Form: LIQUID
Manufacturer: AMERICAN SALES COMPANY
Category: otc | Type: HUMAN OTC DRUG LABEL
Date: 20120927

ACTIVE INGREDIENTS: TRICLOSAN 3 mg/1 mL
INACTIVE INGREDIENTS: WATER BUFFALO; SODIUM XYLENESULFONATE; GLYCERIN; DIPROPYLENE GLYCOL; COCAMIDOPROPYL BETAINE; SODIUM LAURETH SULFATE; SODIUM PHOSPHATE, DIBASIC, ANHYDROUS; METHYLPARABEN; PROPYLPARABEN; POLYSORBATE 20; SODIUM PYRROLIDONE CARBOXYLATE; POLYQUATERNIUM-10 (400 CPS AT 2%); .ALPHA.-TOCOPHEROL ACETATE; CITRIC ACID MONOHYDRATE; CETYL ALCOHOL; D&C RED NO. 33; D&C ORANGE NO. 4

DRUG FACTS

ACTIVE INGREDIENT

TRICLOSAN 0.3%

PURPOSE

ANTIBACTERIAL

USES

FOR WASHING TO DECREASE BACTERIA ON THE SKIN.

WARNINGS

WHEN USING

STOP USING THIS PRODUCT AND ASK DOCTOR

KEEP OUT OF REACH OF CHILDREN

IN CASE OF ACCIDENTAL INGESTION, GET MEDICAL HELP OR CONTACT A POISON CONTROL CENTER IMMEDIATELY.

DIRECTIONS

APPLY TO DRY HANDS, WORK INTO A RICH FOAMY LATHER AND RINSE THOROUGHLY.

INACTIVE INGREDIENT

WATER, SODIUM XYLENESULFONATE, GLYCERIN, DIPROPYLENE GLYCOL, COCAMIDOPROPYL BETAINE, SODIUM LAURETH SULFATE, DISODIUM PHOSPHATE, FRAGRANCE (PARFUM), METHYLPARABEN, PROPYLPARABEN, POLYSORBATE-20, SODIUM PCA, POLYQUATERNIUM-10, TOCOPHERYL ACETATE, CITRIC ACID, CETYL ALCOHOL, RED 33 (CI 17200), ORANGE 4 (CI 15510).